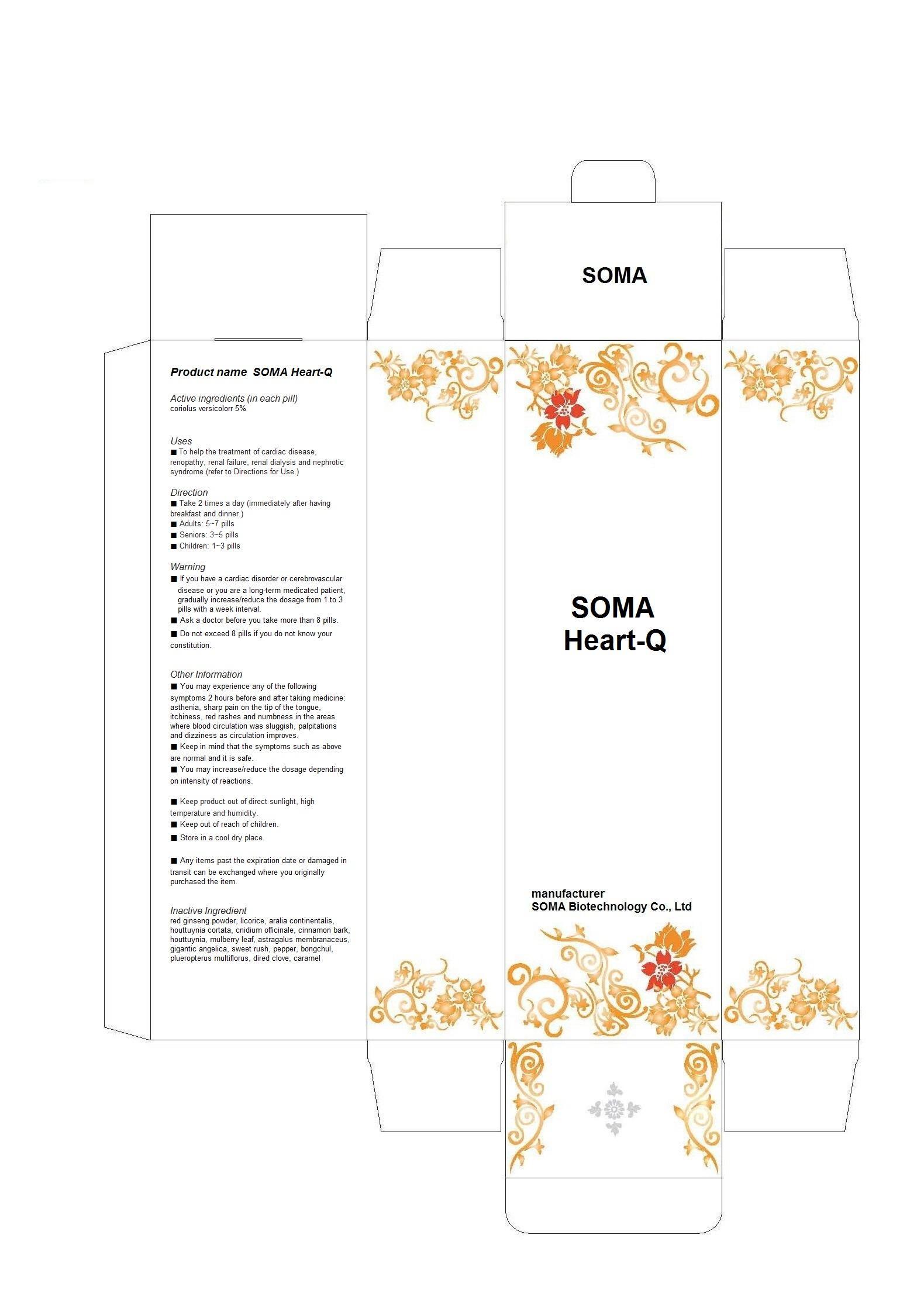 DRUG LABEL: SOMA Heart-Q
NDC: 58370-6001 | Form: PILL
Manufacturer: SOMA Biotechnology Co., Ltd
Category: otc | Type: HUMAN OTC DRUG LABEL
Date: 20130506

ACTIVE INGREDIENTS: TRAMETES VERSICOLOR FRUITING BODY 0.05 g/1 g
INACTIVE INGREDIENTS: ASIAN GINSENG; GLYCYRRHIZA GLABRA; ARALIA CORDATA ROOT; HOUTTUYNIA CORDATA FLOWERING TOP; CNIDIUM OFFICINALE WHOLE; CINNAMON; MORUS AUSTRALIS LEAF; ASTRAGALUS PROPINQUUS ROOT; ANGELICA SINENSIS ROOT; ACORUS GRAMINEUS ROOT; PEPPERS; ZEDOARY; POLYGONUM CUSPIDATUM WHOLE; CLOVE; CARAMEL

Drug Facts

ACTIVE INGREDIENT

coriolus versicolorr

INACTIVE INGREDIENT

red ginseng powder, licorice, aralia continentalis, houttuynia cortata, cnidium officinale, cinnamon bark, houttuynia, mulberry leaf, astragalus membranaceus, gigantic angelica, sweet rush, pepper, bongchul, plueropterus multiflorus, dired clove, caramel

PURPOSE

to help the treatment of cardiac disease, renopathy, renal failure, renal dialysis and nephrotic syndrome

keep out of reach of the children

INDICATIONS AND USAGE

- Take 2 times a day
- adults 5~7 pills
- seniors: 3~5 pills
- children: 1~3 pills

■ do not use if having a cardiac disorder
■ Ask a doctor before taking more than 8 pills

DOSAGE AND ADMINISTRATION

for oral use only